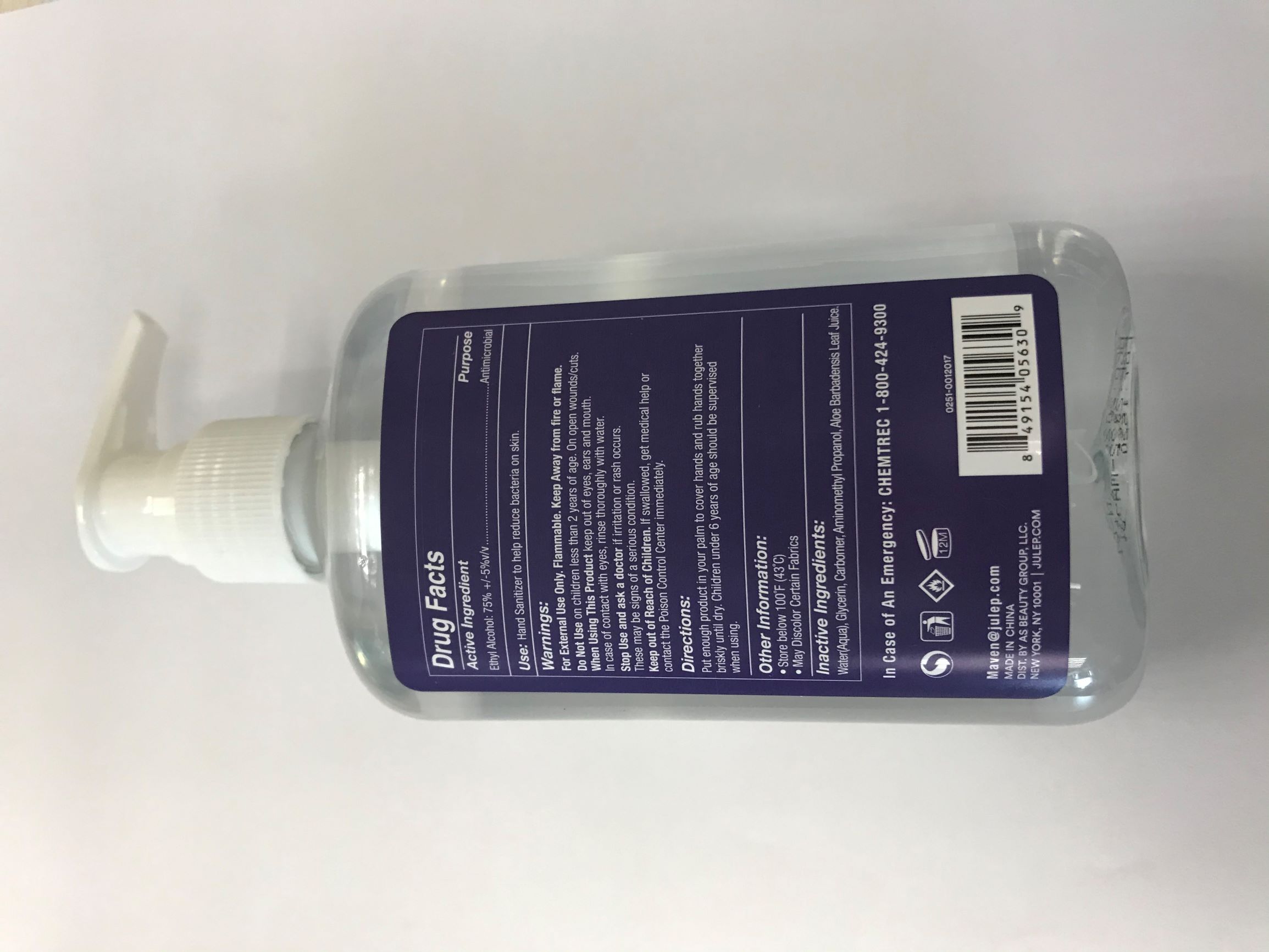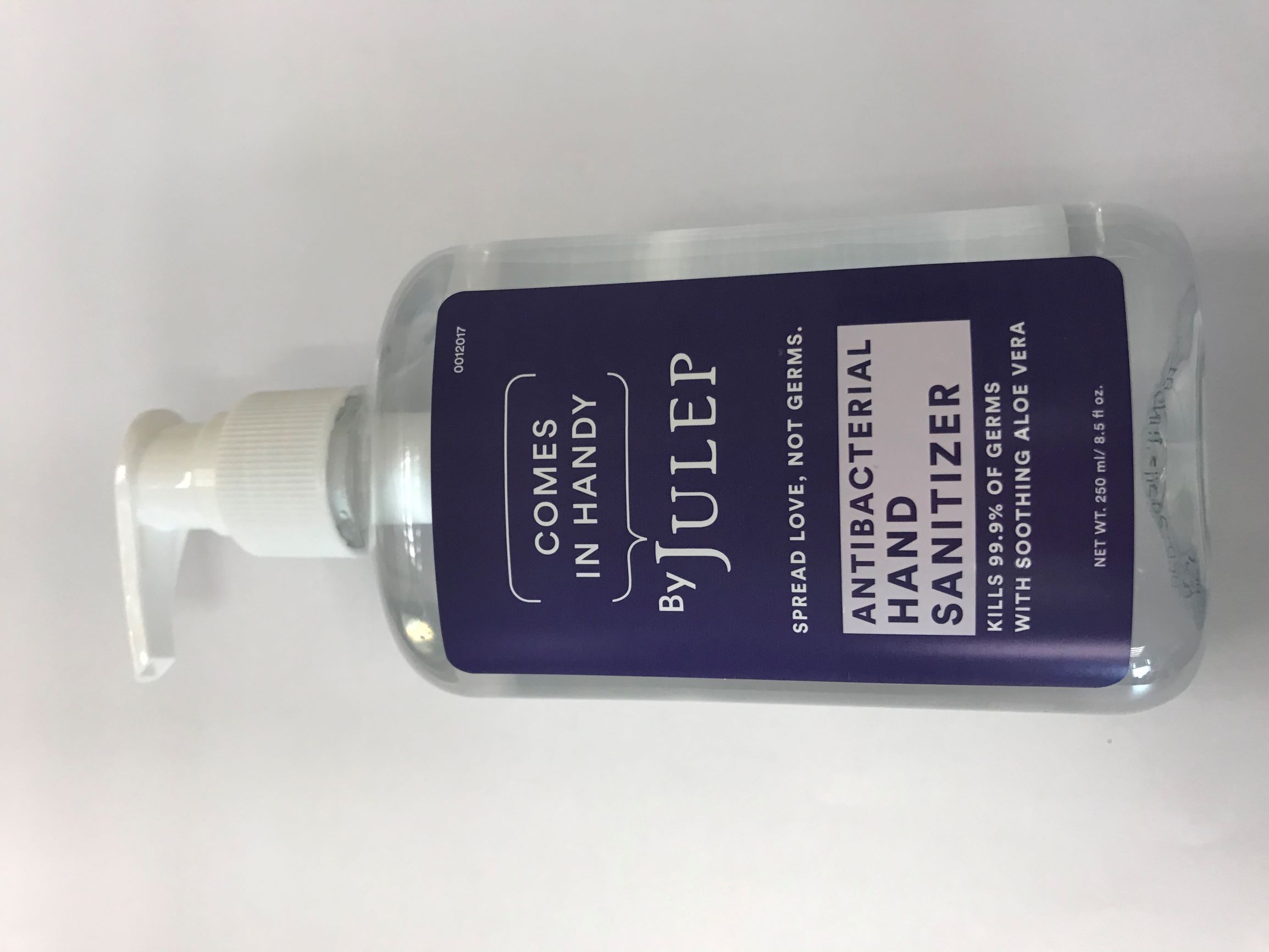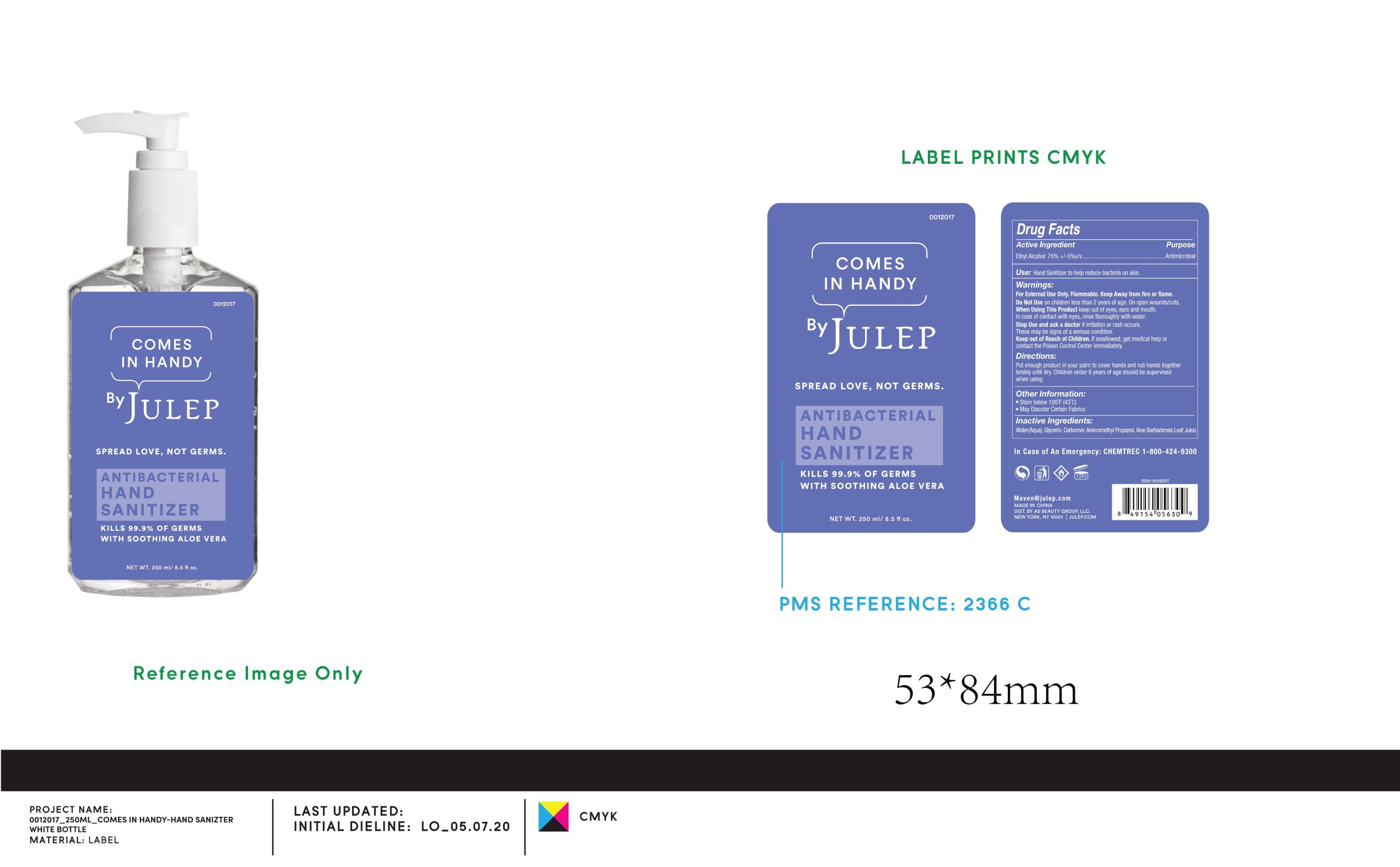 DRUG LABEL: HAND SANITIZER
NDC: 56084-026 | Form: GEL
Manufacturer: Zhejiang RIFESHOW Cosmetics Co., Ltd.
Category: otc | Type: HUMAN OTC DRUG LABEL
Date: 20200828

ACTIVE INGREDIENTS: ALCOHOL 75 mL/100 mL
INACTIVE INGREDIENTS: WATER; CARBOXYPOLYMETHYLENE; ALOE VERA LEAF; GLYCERIN; AMINOMETHYLPROPANOL

Zhejiang RIFESHOW Cosmetics Co., Ltd.
HAND SANITIZER 250ml
56084-026-01

Active Ingredient(s)

Ethyl Alcohol: 75% +/-5% v/v

Purpose

Antimicrobial

Use

Hand Sanitizer to help reduce bacteria on skin.

Warnings

- For External Use Only.
- Flammable. Keep Away from fire or flame.

Do not use

- on children less than 2 years of age.
- on open wounds/cuts.

When Using This Product keep out of eyes, ears and mouth. In case of contact with eyes, rinse thoroughly with water.

Stop Use and ask a doctor if irritation or rash occurs.
These may be signs of a serious condition.

Keep out of Reach of Children. If swallowed, get medical help or contact the Posion Control Center immediately.

Directions

Put enough product in your palm to cover hands and rub hands together briskly until dry. Children under 6 years of age should be supervised when using.

Other information

- Store below 100℉(43℃)
- May Discolor Certain Fabrics

Inactive ingredients

Water(Aqua), Glycerin, Carbomer, Aminomethyl Propanol, Aloe Barbadensis Leaf Juice.

Package Label - Principal Display Panel

250 mL NDC: 56084-026-01